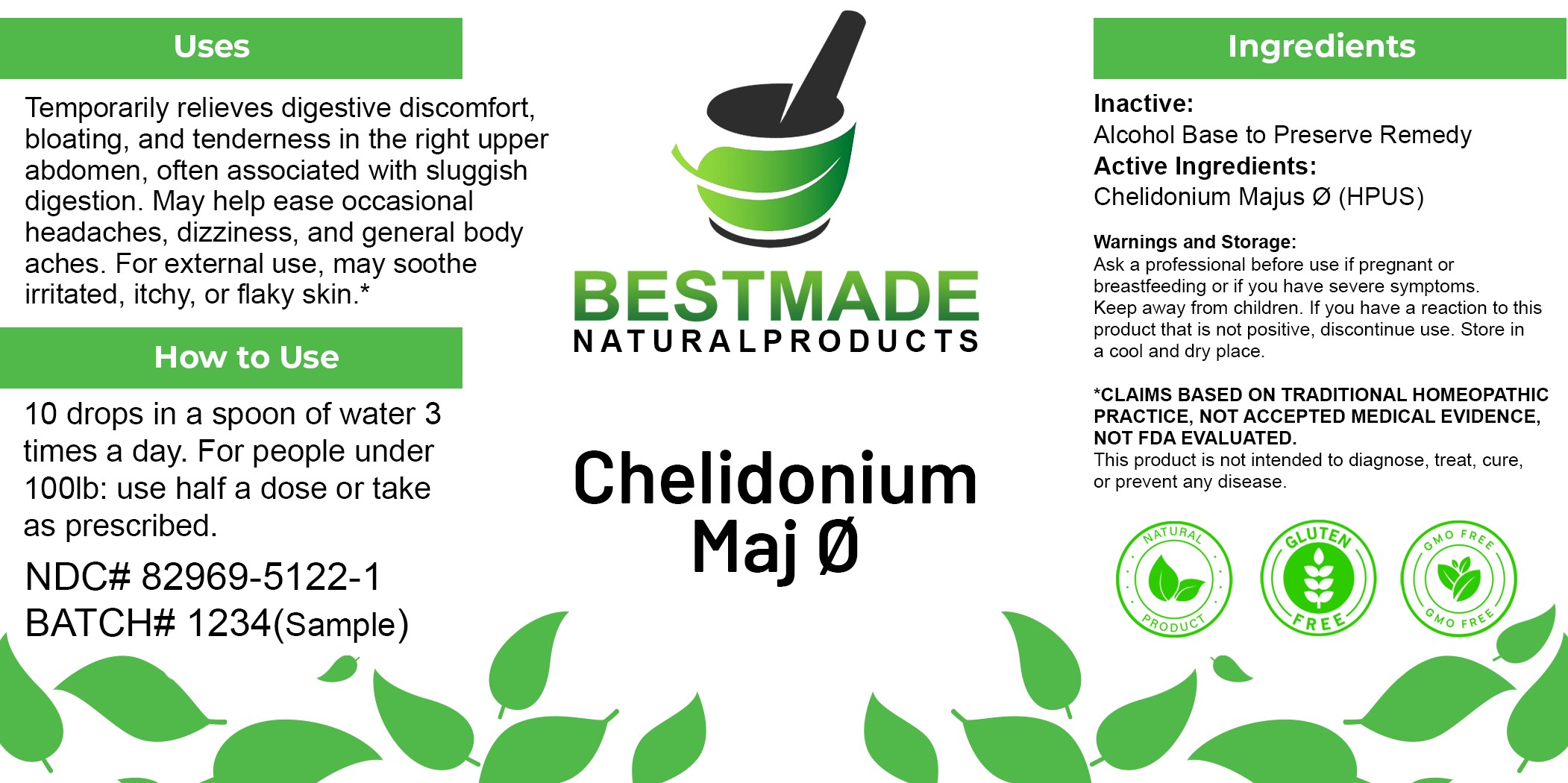 DRUG LABEL: Bestmade Natural Products Chelidonium Maj
NDC: 82969-5122 | Form: TINCTURE
Manufacturer: Bestmade Natural Products
Category: homeopathic | Type: HUMAN OTC DRUG LABEL
Date: 20250605

ACTIVE INGREDIENTS: CHELIDONIUM MAJUS WHOLE 1 [hp_M]/1 mL
INACTIVE INGREDIENTS: ALCOHOL 0.7 mL/1 mL; WATER 0.3 mL/1 mL

Chelidonium Maj Ø

Inactive Ingredient: Alcohol base to preserve product.

DOSAGE AND ADMINISTRATION

Dosage Instructions: 10 drops in a spoon of water 3 times a day. For people under 100lb: use half a dose or take as prescribed.

PURPOSE

Use: Temporarily relieves digestive discomfort, bloating, and tenderness in the right upper abdomen, often associated with sluggish digestion. May help ease occasional headaches, dizziness, and general body aches. For external use, may soothe irritated, itchy, or flaky skin.*

INDICATIONS AND USAGE

Use: Temporarily relieves digestive discomfort, bloating, and tenderness in the right upper abdomen, often associated with sluggish digestion. May help ease occasional headaches, dizziness, and general body aches. For external use, may soothe irritated, itchy, or flaky skin.*

Active Ingredient: Chelidonium Majus Ø (HPUS)

KEEP OUT OF REACH OF CHILDREN

Warnings and Storage:

Ask a professional before use if pregnant or breastfeeding or if you have severe symptoms. Keep away from children. If you have a reaction to this product that is not positive, discontinue use. Store in a cool and dry place.

*CLAIMS BASED ON TRADITIONAL HOMEOPATHIC PRACTICE, NOT ACCEPTED MEDICAL EVIDENCE, NOT FDA EVALUATED. This product is not intended to diagnose, treat, cure, or prevent any disease.

Warnings and Storage:

Ask a professional before use if pregnant or breastfeeding or if you have severe symptoms. Keep away from children. If you have a reaction to this product that is not positive, discontinue use. Store in a cool and dry place.

*CLAIMS BASED ON TRADITIONAL HOMEOPATHIC PRACTICE, NOT ACCEPTED MEDICAL EVIDENCE, NOT FDA EVALUATED. This product is not intended to diagnose, treat, cure, or prevent any disease.

Entire Package Label